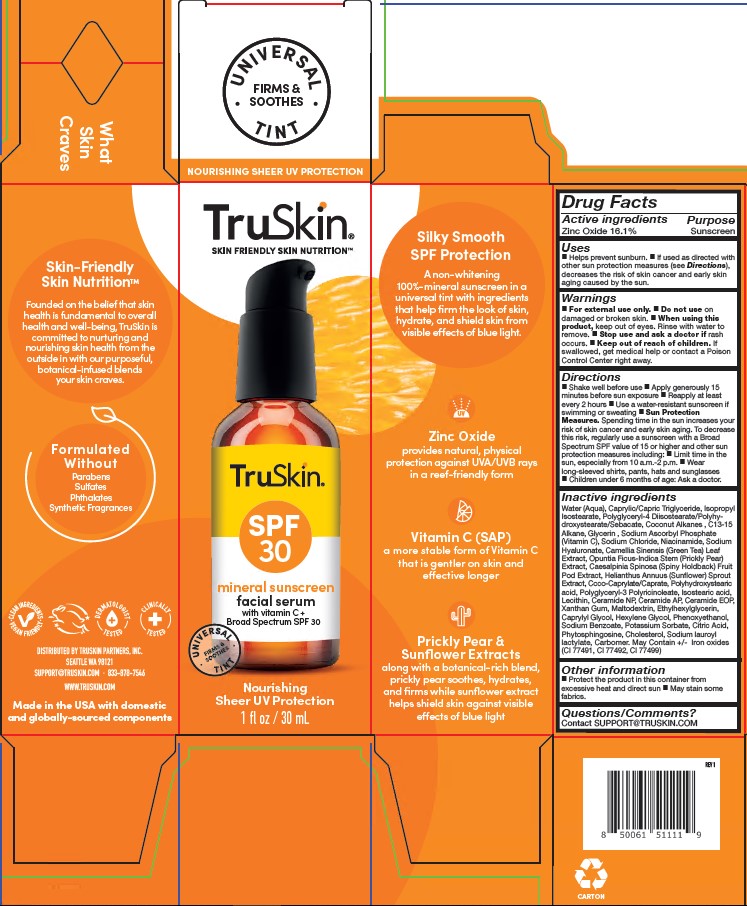 DRUG LABEL: Truskin SPF 30 Mineral Sunscreen Facial Serum
NDC: 62742-4269 | Form: CREAM
Manufacturer: Allure Labs
Category: otc | Type: HUMAN OTC DRUG LABEL
Date: 20260225

ACTIVE INGREDIENTS: ZINC OXIDE 16.1 g/100 g
INACTIVE INGREDIENTS: CAESALPINIA SPINOSA FRUIT POD; HELIANTHUS ANNUUS SPROUT; COCONUT ALKANES; POLYGLYCERYL-3 PENTARICINOLEATE; LECITHIN, SUNFLOWER; CERAMIDE AP; HEXYLENE GLYCOL; CARBOMER; SODIUM BENZOATE; GREEN TEA LEAF; CAPRYLYL GLYCOL; CHOLESTEROL; SODIUM CHLORIDE; ISOPROPYL ISOSTEARATE; POLYGLYCERYL-4 DIISOSTEARATE/POLYHYDROXYSTEARATE/SEBACATE; OPUNTIA FICUS-INDICA STEM; CI 77491; XANTHAN GUM; CI 77492; SODIUM LAUROYL LACTYLATE; POTASSIUM SORBATE; CITRIC ACID; WATER; GLYCERIN; SODIUM ASCORBYL PHOSPHATE; CERAMIDE NP; PHENOXYETHANOL; NIACINAMIDE; SODIUM HYALURONATE; CI 77499; PHYTOSPHINGOSINE; POLYHYDROXYSTEARIC ACID (2300 MW); ISOSTEARIC ACID; CAPRYLIC/CAPRIC TRIGLYCERIDE; C13-15 ALKANE; COCO-CAPRYLATE/CAPRATE; ETHYLHEXYLGLYCERIN; MALTODEXTRIN

Drug Facts

Active ingredients: Zinc Oxide 16.1%

Purpose: Sunscreen

INDICATIONS AND USAGE

Uses ■ Helps prevent sunburn. ■ If used as directed with other sun protection measures (see Directions), decreases the risk of skin cancer and early skin aging caused by the sun.

WARNINGS

For external use only.

Do not use on damaged or broken skin.

when using this product, keep out of eyes. Rinse with water to remove.

Stop use and ask a doctor if rash occurs.

keep out of reach of children. If swallowed, get medical help or contact a Poison Control Center right away.

DOSAGE AND ADMINISTRATION

Directions ■ Shake well before use ■ Apply generously 15 minutes before sun exposure ■ Reapply at least every 2 hours ■ Use a water-resistant sunscreen if swimming or sweating ■ Sun Protection Measures Spending time in the sun increases your risk of skin cancer and early skin aging. To decrease this risk, regularly use sunscreen with a Broad Spectrum SPF value of 15 or higher and other sun protection measures including ■ Limit time in the sun, especially from 10 a.m.-2 p.m. ■ Wear long-sleeved shirts, pants hats and sunglasses ■ Children under 6 months of age: Ask a doctor.

OTHER SAFETY INFORMATION

Protect the product in this container from excessive heat and direct sun. May stain some fabrics.

Inactive Ingredients:
Water(Aqua),Caprylic/capric Triglyceride, Isopropyl Isostearate, Polyglyceryl -4 Diisostearate/Polyhydroxy stearate/sebacate, Coconut Alkanes, C13-15 Alkane, Glycerin, Sodium Ascorbyl Phosphate (Vitamin C), Sodium Chloride, Niacinamide, Sodium Hyaluronate, Camellia Sinensis (Green Tea) Leaf Extract, Opuntia Ficus-Indica Stem (Prickly Pear)Extract, Caesalpinia Spinosa (Spiny Holdback) Fruit Pod Extract, Helianthus Annuus (Sunflower) Sprout Extract, Coco-Caprylate/-Caprate, Polyhydroxystearic acid, Polyglyceryl – 3 Polyricinoleate, Isosteric acid, Lecithin, Ceramide NP, Ceramide AP, Ceramide EOP, Xanthan Gum, Maltodextrin, Ethylhexylglycerin, Caprylyl Glycol, Hexylene Glycol, Phenoxyethanol, Sodium Benzoate, Potassium Sorbate, Citric Acid, Phytosphingosine, Cholesterol, Sodium lauroyl lactylate, Carbomer. May Contain +/_ Iron oxides (CI77491, CI77492, CI 77499)